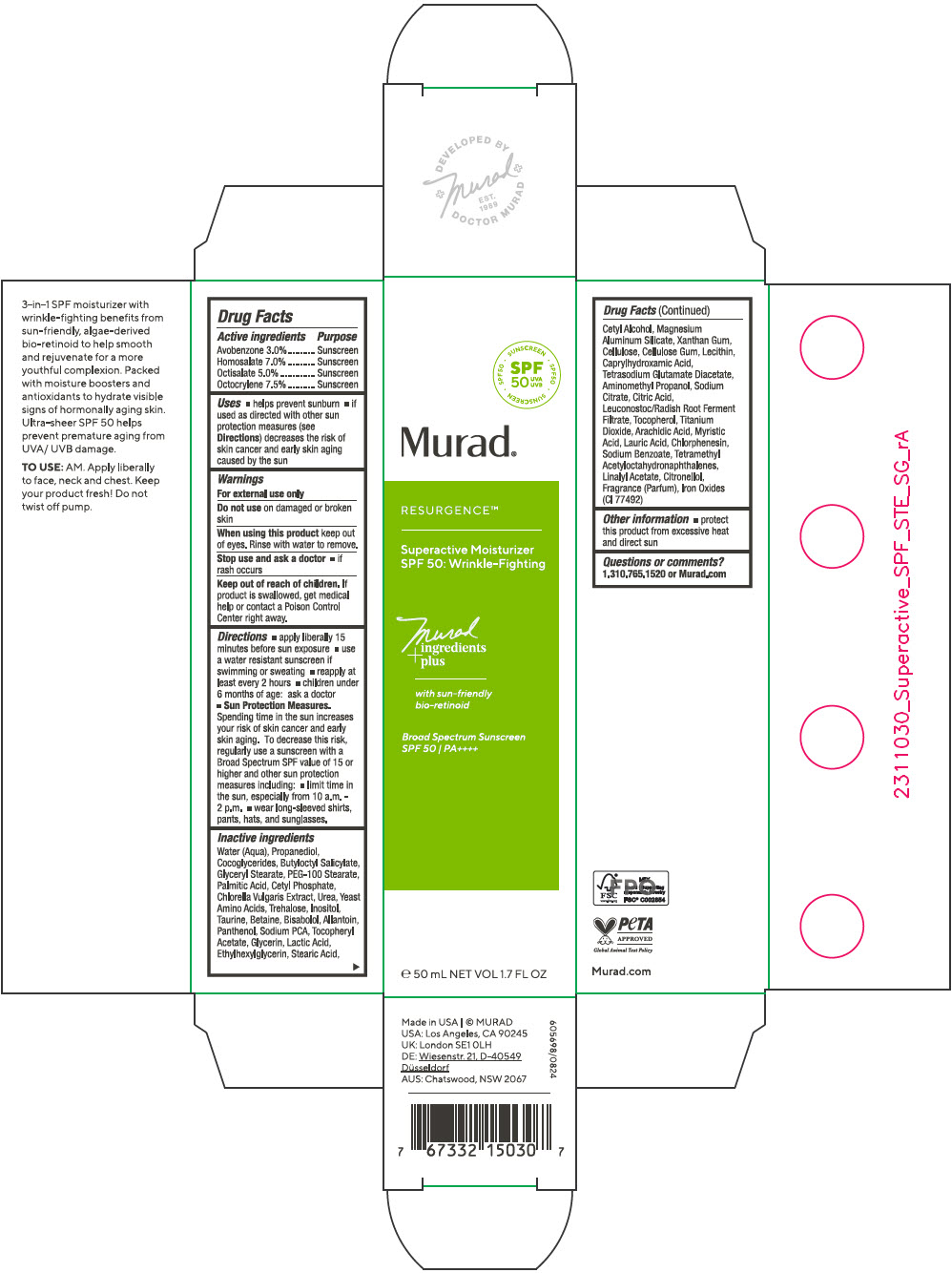 DRUG LABEL: Superactive Moisturizer SPF 50 Wrinkle Fighting
NDC: 70381-131 | Form: CREAM
Manufacturer: Murad, LLC
Category: otc | Type: HUMAN OTC DRUG LABEL
Date: 20250326

ACTIVE INGREDIENTS: AVOBENZONE 3 g/100 mL; HOMOSALATE 7 g/100 mL; OCTISALATE 5 g/100 mL; OCTOCRYLENE 7.5 g/100 mL
INACTIVE INGREDIENTS: WATER; PROPANEDIOL; COCO-GLYCERIDES; BUTYLOCTYL SALICYLATE; GLYCERYL MONOSTEARATE; PEG-100 STEARATE; PALMITIC ACID; CETYL PHOSPHATE; CHLORELLA VULGARIS; UREA; AMINO ACIDS, SOURCE UNSPECIFIED; TREHALOSE; INOSITOL; TAURINE; BETAINE; LEVOMENOL; ALLANTOIN; PANTHENOL; SODIUM PYRROLIDONE CARBOXYLATE; .ALPHA.-TOCOPHEROL ACETATE; GLYCERIN; LACTIC ACID, UNSPECIFIED FORM; ETHYLHEXYLGLYCERIN; STEARIC ACID; CETYL ALCOHOL; MAGNESIUM ALUMINUM SILICATE; XANTHAN GUM; POWDERED CELLULOSE; CARBOXYMETHYLCELLULOSE SODIUM, UNSPECIFIED; SOYBEAN LECITHIN; CAPRYLHYDROXAMIC ACID; TETRASODIUM GLUTAMATE DIACETATE; AMINOMETHYLPROPANOL; TRISODIUM CITRATE DIHYDRATE; CITRIC ACID MONOHYDRATE; LEUCONOSTOC/RADISH ROOT FERMENT FILTRATE; TOCOPHEROL; TITANIUM DIOXIDE; ARACHIDIC ACID; MYRISTIC ACID; LAURIC ACID; CHLORPHENESIN; SODIUM BENZOATE; TETRAMETHYL ACETYLOCTAHYDRONAPHTHALENES; LINALYL ACETATE; .BETA.-CITRONELLOL, (R)-; FERRIC OXIDE YELLOW

Superactive Moisturizer SPF 50: Wrinkle-Fighting
SPF 50

Drug Facts

ACTIVE INGREDIENT

Active ingredients | Purpose
Avobenzone 3.0% | Sunscreen
Homosalate 7.0% | Sunscreen
Octisalate 5.0% | Sunscreen
Octocrylene 7.5% | Sunscreen

Uses

- helps prevent sunburn
- if used as directed with other sun protection measures (see Directions) decreases the risk of skin cancer and early skin aging caused by the sun

Warnings

For external use only

Do not use on damaged or broken skin

When using this product keep out of eyes. Rinse with water to remove.

Stop use and ask a doctor

- if rash occurs

Keep out of reach of children. If product is swallowed, get medical help or contact a Poison Control Center right away.

Directions

- apply liberally 15 minutes before sun exposure
- use a water resistant sunscreen if swimming or sweating
- reapply at least every 2 hours
- children under 6 months of age: ask a doctor
- Sun Protection Measures. Spending time in the sun increases your risk of skin cancer and early skin aging. To decrease this risk, regularly use a sunscreen with a Broad Spectrum SPF value of 15 or higher and other sun protection measures including:
  - limit time in the sun, especially from 10 a.m. - 2 p.m.
  - wear long-sleeved shirts, pants, hats, and sunglasses.

Inactive ingredients

Water (Aqua), Propanediol, Cocoglycerides, Butyloctyl Salicylate, Glyceryl Stearate, PEG-100 Stearate, Palmitic Acid, Cetyl Phosphate, Chlorella Vulgaris Extract, Urea, Yeast Amino Acids, Trehalose, Inositol, Taurine, Betaine, Bisabolol, Allantoin, Panthenol, Sodium PCA, Tocopheryl Acetate, Glycerin, Lactic Acid, Ethylhexylglycerin, Stearic Acid, Cetyl Alcohol, Magnesium Aluminum Silicate, Xanthan Gum, Cellulose, Cellulose Gum, Lecithin, Caprylhydroxamic Acid, Tetrasodium Glutamate Diacetate, Aminomethyl Propanol, Sodium Citrate, Citric Acid, Leuconostoc/Radish Root Ferment Filtrate, Tocopherol, Titanium Dioxide, Arachidic Acid, Myristic Acid, Lauric Acid, Chlorphenesin, Sodium Benzoate, Tetramethyl Acetyloctahydronaphthalenes, Linalyl Acetate, Citronellol, Fragrance (Parfum), Iron Oxides (CI 77492)

Other information

- protect this product from excessive heat and direct sun

Questions or comments?

1.310.765.1520 or Murad.com

PRINCIPAL DISPLAY PANEL - 50 mL Bottle Carton

SPF
50
UVA
UVB

SUNSCREEN • SPF50 • SUNSCREEN • SPF50 •

Murad®

RESURGENCE™

Superactive Moisturizer
SPF 50: Wrinkle-Fighting

Murad
ingredients
+plus

with sun-friendly
bio-retinoid

Broad Spectrum Sunscreen
SPF 50 / PA++++

℮ 50 mL NET VOL 1.7 FL OZ